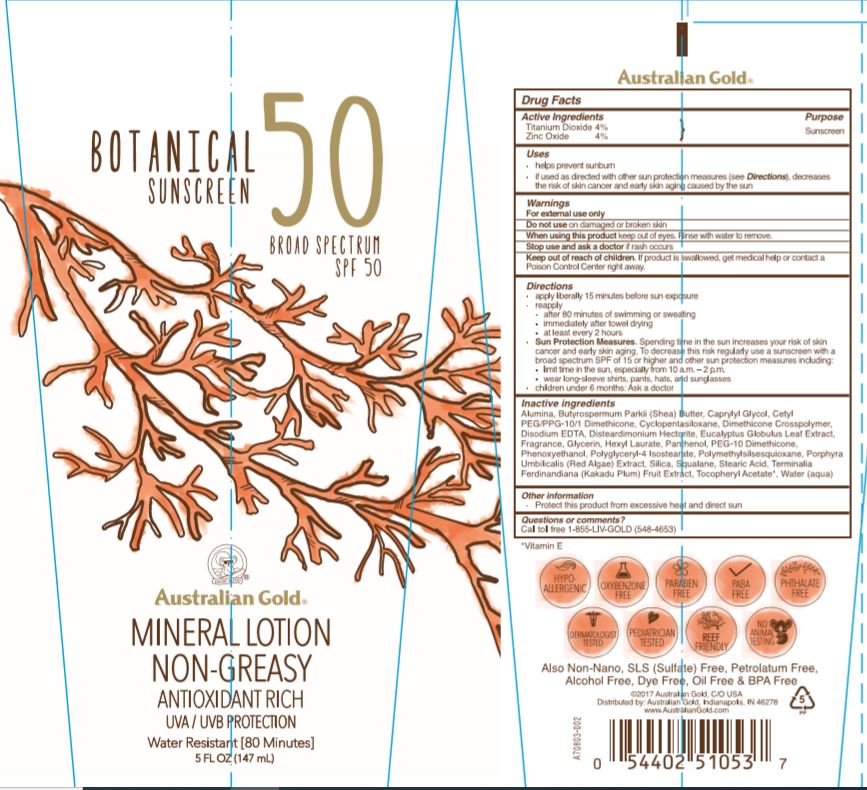 DRUG LABEL: Austalian Gold
NDC: 58443-0319 | Form: LOTION
Manufacturer: Prime Enterprises Inc.
Category: otc | Type: HUMAN OTC DRUG LABEL
Date: 20200511

ACTIVE INGREDIENTS: TITANIUM DIOXIDE 42.8 mg/1 mL; ZINC OXIDE 42.8 mg/1 mL
INACTIVE INGREDIENTS: PANTHENOL; FRAGRANCE LAVENDER & CHIA F-153480; CYCLOMETHICONE 5; ALUMINUM OXIDE; DIMETHICONE CROSSPOLYMER (450000 MPA.S AT 12% IN CYCLOPENTASILOXANE); STEARIC ACID; PEG-10 DIMETHICONE (600 CST); CETYL PEG/PPG-10/1 DIMETHICONE (HLB 2); POLYGLYCERYL-4 ISOSTEARATE; DISTEARDIMONIUM HECTORITE; CAPRYLYL GLYCOL; SQUALANE; SILICON DIOXIDE; POLYMETHYLSILSESQUIOXANE (4.5 MICRONS); PORPHYRA UMBILICALIS; GLYCERIN; KAKADU PLUM; PHENOXYETHANOL; ALPHA-TOCOPHEROL ACETATE; WATER; EUCALYPTUS GLOBULUS LEAF; SHEA BUTTER; EDETATE DISODIUM ANHYDROUS; HEXYL LAURATE

Australian Gold Botanical Sunscreen Broad Spectrum SPF 50

INACTIVE INGREDIENTS

Cyclopentasiloxane, Water, Glycerin, Silica, Cetyl PEG/PPG-10/1 Dimethicone, Disteardimonium Hectorite, Polymethylsilsesquioxane, PEG-10 Dimethicone, Hexyl Laurate, Polyglyceryl-4 Isostearate, Dimethicone Crosspolymer, Fragrance, Stearic Acid, Phenoxyethanol, Alumina, Caprylyl Glycol, Tocopheryl Acetate, Butyrospermum Parkii (Shea) Butter, Panthenol, Squalane, Disodium EDTA, Eucalyptus Globulus (Eucalyptus) Leaf Extract, Porphyra Umbilicalis Extract, Terminalia Ferdinandiana (Kakadu Plum) Fruit Extract

Warnings

For external use only

Do not use on damaged or broken skin.

When using this product keep out of eyes. Rinse with water to remove. Keep away from face to avoid breathing it.

Stop use and ask a doctor if rash occurs.

Keep out of reach of children. If product is swallowed, get medical help or contact a Poison Control Center right away.

Do not use on damaged or broken skin

When using this product keep out of eyes. Rinse with water to remove.

Stop use and ask a doctor if rash occurs

Keep out of reach of children. If product is swallowed, get medical help or contact a Poison Control Center right away.

Purpose

Sunscreen

Uses

- helps prevent sunburn
  - if used as directed with other sun protection measures (see Directions) decreases the risk of skin cancer and early skin aging caused by the sun

Active Ingredients

Titanium Oxide 4%

Zinc Oxide 4%

Directions

- apply liberally 15 minutes before sun exposure and rub into skin
- reapply:
- after 80 minutes of swimming or sweating
- immediately after towel drying
- at least every 2 hours
- Sun Protection Measures Spending time ine the sun increases your risk of skin cancer and early skin aging. To decrease this risk, regularly use a sunscreen with a broad spectrum SPF valvue of 15 or higher and other sun protecion measures including:
- limit tim ein the sun, especially from 10am-2pm
- wear long sleeve shirts, pants, hats, and sunglasses
- children under 6 months: Ask a doctor

Other Information

Protect this product from excessive heat and direct sun

Questions or Comments?

Call Toll free 1-855-LIV-GOLD (548-4653)